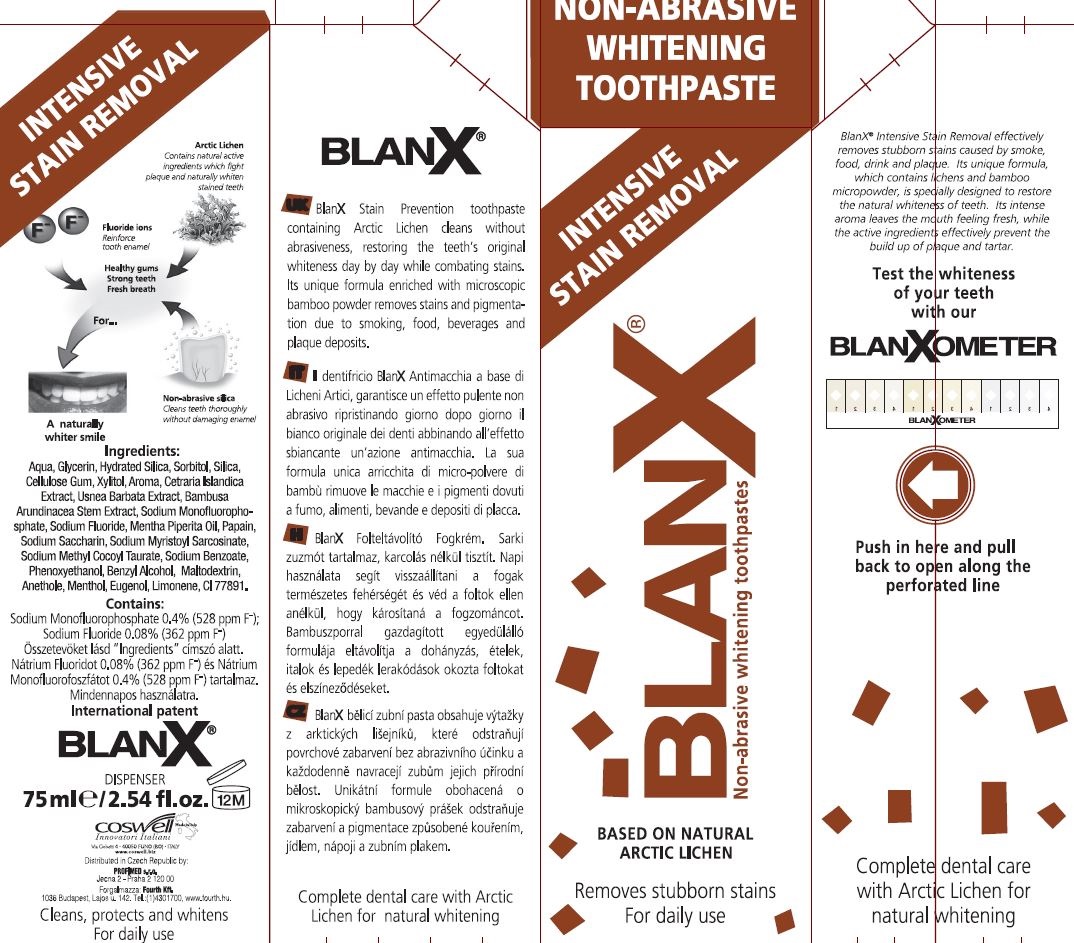 DRUG LABEL: BlanX Intensive Stain Removal
NDC: 70781-003 | Form: PASTE
Manufacturer: Coswell Spa
Category: otc | Type: HUMAN OTC DRUG LABEL
Date: 20190204

ACTIVE INGREDIENTS: SODIUM FLUORIDE 0.002 g/100 g; SODIUM MONOFLUOROPHOSPHATE 0.01 g/100 g
INACTIVE INGREDIENTS: MENTHOL, UNSPECIFIED FORM; PEPPERMINT OIL; ANETHOLE; SILICON DIOXIDE; SODIUM METHYL COCOYL TAURATE; XYLITOL; SODIUM MYRISTOYL SARCOSINATE; EUGENOL; LIMONENE, (+)-; TITANIUM DIOXIDE; BENZYL ALCOHOL; PHENOXYETHANOL; SACCHARIN SODIUM; SODIUM BENZOATE; CARBOXYMETHYLCELLULOSE SODIUM; GLYCERIN; CETRARIA ISLANDICA SUBSP. ISLANDICA; WATER; SORBITOL; HYDRATED SILICA; BAMBUSA BAMBOS STEM; PAPAIN; USNEA BARBATA; MALTODEXTRIN

BlanX Intensive Stain Removal

ACTIVE INGREDIENT

Contains:

Sodium Monofluorophosphate 0.4% (528 ppm F)

Sodium Fluoride 0.08% (362 ppm F)

INACTIVE INGREDIENT

Ingredients:

Aqua, Glycerin, Hydrated Silica, Sorbitol, Silica, Cellulose Gum, Xylitol, Aroma, Cetraria Islandica Extract, Usnea Barbata Extract, Bambusa Arundinacea Stem Extract, Sodium Monofluorophosphate, Sodium Fluoride, Mentha Piperita Oil, Papain, Sodium Saccharin, Sodium Myristoyl Sarcosinate, Sodium Methyl Cocoyl Taurate, Sodium Benzoate, Phenoxyethanol, Benzyl Alcohol, Maltodextrin, Anethol, Menthol, Eugenol, Limonene, CI 77891.

PURPOSE

Non-Abrasive Whitening Toothpaste

Intensive Stain Removal

Removes stubborn stains

For daily use

Complete dental care with Arctic Lichen for natural whitening

BlanX Stain Prevention toothpaste containing Arctic Lichen cleans without abrasiveness, restoring the teeth's original whiteness day by day while combatin stains. Its unique formula enriched with microscopic bamboo powder removes stains and pigmentation due to smoking, food, beverages and plaque deposits.

Keep out of reach of children

DOSAGE AND ADMINISTRATION

For daily use

INDICATIONS AND USAGE

For daily use

Warnings